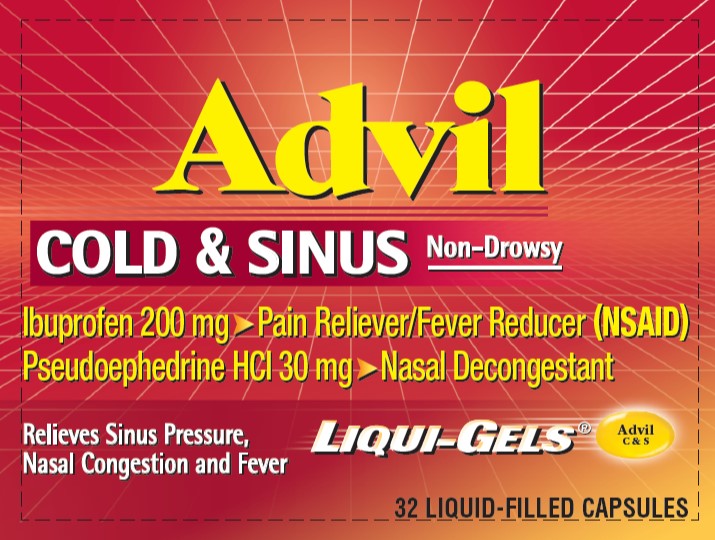 DRUG LABEL: ADVIL COLD AND SINUS
NDC: 0573-0184 | Form: CAPSULE, LIQUID FILLED
Manufacturer: Haleon US Holdings LLC
Category: otc | Type: HUMAN OTC DRUG LABEL
Date: 20250911

ACTIVE INGREDIENTS: IBUPROFEN 200 mg/1 1; PSEUDOEPHEDRINE HYDROCHLORIDE 30 mg/1 1
INACTIVE INGREDIENTS: D&C YELLOW NO. 10; FD&C RED NO. 40; GELATIN, UNSPECIFIED; MEDIUM-CHAIN TRIGLYCERIDES; POLYETHYLENE GLYCOL, UNSPECIFIED; POTASSIUM HYDROXIDE; WATER; SORBITOL; SORBITAN

Drug Facts

Active ingredients (in each liquid-filled capsule)

Solubilized ibuprofen equal to 200 mg ibuprofen (NSAID)*

(present as the free acid and potassium salt)

Pseudoephedrine HCl 30 mg

*nonsteroidal anti-inflammatory drug

Purposes

Pain reliever/fever reducer

Nasal decongestant

Uses

temporarily relieves these symptoms associated with the common cold or flu:

- headache
- fever
- sinus pressure
- nasal congestion
- minor body aches and pains

Warnings

Allergy alert: Ibuprofen may cause a severe allergic reaction, especially in people allergic to aspirin. Symptoms may include:

- hives
- facial swelling
- asthma (wheezing)
- shock
- skin reddening
- rash
- blisters

If an allergic reaction occurs, stop use and seek medical help right away.

Stomach bleeding warning: This product contains an NSAID, which may cause severe stomach bleeding. The chance is higher if you:

- are age 60 or older
- have had stomach ulcers or bleeding problems
- take a blood thinning (anticoagulant) or steroid drug
- take other drugs containing prescription or nonprescription NSAIDs [aspirin, ibuprofen, naproxen, or others]
- have 3 or more alcoholic drinks every day while using this product
- take more or for a longer time than directed

Do not use

- in children under 12 years of age
- if you have ever had an allergic reaction to any other pain reliever/fever reducer
- right before or after heart surgery
- if you are now taking a prescription monoamine oxidase inhibitor (MAOI) (certain drugs for depression, psychiatric, or emotional conditions, or Parkinson's disease), or for 2 weeks after stopping the MAOI drug. If you do not know if your prescription drug contains an MAOI, ask a doctor or pharmacist before taking this product.

Ask a doctor before use if

- stomach bleeding warning applies to you
- you have problems or serious side effects from taking pain relievers or fever reducers
- you have a history of stomach problems, such as heartburn
- you have high blood pressure, heart disease, liver cirrhosis, kidney disease, asthma, thyroid disease, diabetes, have trouble urinating due to an enlarged prostate gland, or had a stroke
- you are taking a diuretic

Ask a doctor or pharmacist before use if you are

- under a doctor's care for any serious condition
- taking any other product that contains pseudoephedrine or any other nasal decongestant
- taking aspirin for heart attack or stroke, because ibuprofen may decrease this benefit of aspirin
- taking any other drug

When using this product

- take with food or milk if stomach upset occurs

Stop use and ask a doctor if

- you experience any of the following signs of stomach bleeding:
  - feel faint
  - vomit blood
  - have bloody or black stools
  - have stomach pain that does not get better
- you have symptoms of heart problems or stroke:
  - chest pain
  - trouble breathing
  - weakness in one part or side of body
  - slurred speech
  - leg swelling
- fever gets worse or lasts more than 3 days
- nasal congestion lasts for more than 7 days
- symptoms continue or get worse
- redness or swelling is present in the painful area
- you get nervous, dizzy, or sleepless
- any new symptoms appear

If pregnant or breast-feeding,

ask a health professional before use. It is especially important not to use ibuprofen at 20 weeks or later in pregnancy unless definitely directed to do so by a doctor because it may cause problems in the unborn child or complications during delivery.

Directions

- do not take more than directed
- the smallest effective dose should be used
- adults and children 12 years of age and over:
  - take 1 capsule every 4 to 6 hours while symptoms persist. If symptoms do not respond to 1 capsule, 2 capsules may be used.
  - do not use more than 6 capsules in any 24-hour period unless directed by a doctor
- children under 12 years of age: do not use

Other information

- each capsule contains: potassium 20 mg
- store at 20-25°C (68-77°F). Avoid excessive heat above 40°C (104°F).
- read all warnings and directions before use. Keep carton.

Inactive ingredients

D&C yellow no. 10, FD&C red no. 40, gelatin, medium-chain triglycerides, pharmaceutical ink, polyethylene glycol, potassium hydroxide, purified water, sorbitol sorbitan solution

Questions or comments?

Call weekdays from 9 AM to 5 PM ESTtoll free at 1-800-88-ADVIL

Additional Information

READ AND KEEP CARTON FOR COMPLETE

WARNINGS AND INFORMATION

Product inside sealed in plastic blister with foil backing.
Do Not Use if plastic blister or foil barrier is broken.

For most recent product information,
visit www.advil.com

PRINCIPAL DISPLAY PANEL

Advil

COLD & SINUS Non-Drowsy

Ibuprofen 200 mg ‣ Pain Reliever/Fever Reducer (NSAID)

Pseudoephedrine HCl 30 mg ‣ Nasal Decongestant

Relieves Sinus Pressure,
Nasal Congestion and Fever

LIQUI-GELS®

Advil
C & S

32 LIQUID-FILLED CAPSULES

000065783 Carton